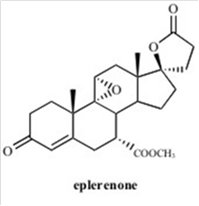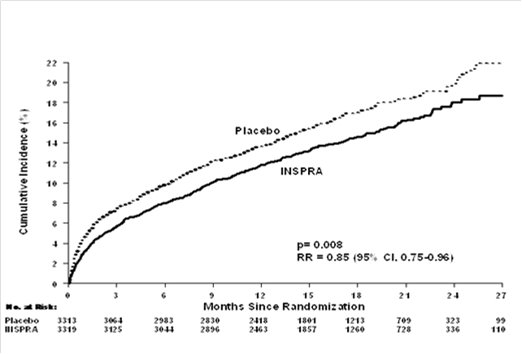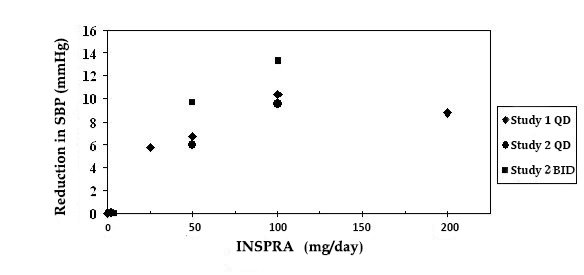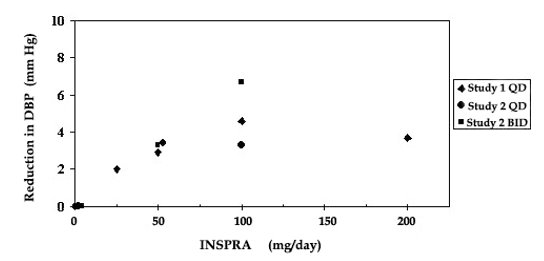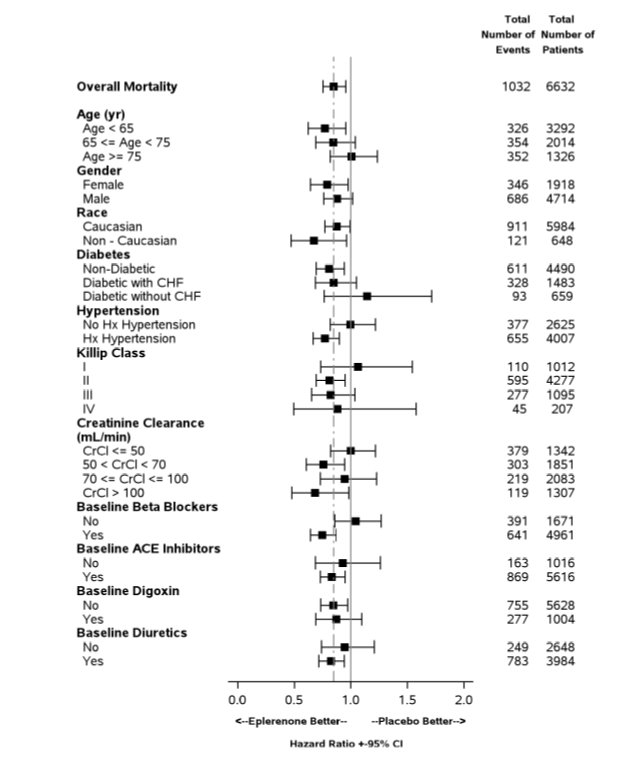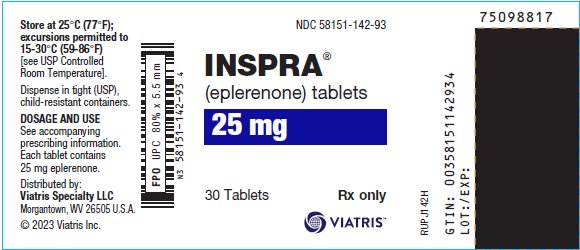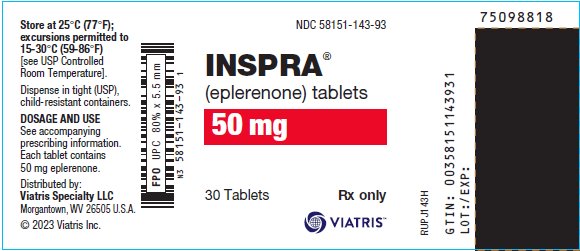 DRUG LABEL: Inspra
NDC: 58151-142 | Form: TABLET, FILM COATED
Manufacturer: Viatris Specialty LLC
Category: prescription | Type: HUMAN PRESCRIPTION DRUG LABEL
Date: 20250623

ACTIVE INGREDIENTS: EPLERENONE 25 mg/1 1
INACTIVE INGREDIENTS: LACTOSE, UNSPECIFIED FORM; MICROCRYSTALLINE CELLULOSE; CROSCARMELLOSE SODIUM; HYPROMELLOSE, UNSPECIFIED; SODIUM LAURYL SULFATE; TALC; MAGNESIUM STEARATE; TITANIUM DIOXIDE; POLYETHYLENE GLYCOL, UNSPECIFIED; POLYSORBATE 80; FERRIC OXIDE YELLOW; FERRIC OXIDE RED

HIGHLIGHTS OF PRESCRIBING INFORMATION

These highlights do not include all the information needed to use INSPRA safely and effectively. See full prescribing information for INSPRA.
INSPRA® (eplerenone) tablets, for oral use
Initial U.S. Approval: 2002

1 INDICATIONS AND USAGE

INSPRA is an aldosterone antagonist indicated for:

- Improving survival of stable adult patients with symptomatic heart failure with reduced ejection fraction (HFrEF) after an acute myocardial infarction. (1.1)
- The treatment of hypertension in adults, to lower blood pressure. Lowering blood pressure reduces the risk of fatal and nonfatal cardiovascular events, primarily strokes and myocardial infarctions. (1.2)

2 DOSAGE AND ADMINISTRATION

HFrEF Post-MI: Initiate treatment with 25 mg once daily. Titrate to maximum of 50 mg once daily within 4 weeks, as tolerated. Dose adjustments may be required based on potassium levels. (2.1)
Hypertension: 50 mg once daily, alone or combined with other antihypertensive agents. For inadequate response, increase to 50 mg twice daily. Higher dosages are not recommended. (2.2)

For all patients:
Measure serum potassium before starting INSPRA and periodically thereafter. (2.3)

3 DOSAGE FORMS AND STRENGTHS

Tablets: 25 mg, 50 mg (3)

4 CONTRAINDICATIONS

For all patients:

- Serum potassium >5.5 mEq/L at initiation (4)
- Creatinine clearance ≤30 mL/min (4)
- Concomitant use with strong CYP3A inhibitors (4, 7.1)

For the treatment of hypertension:

- Type 2 diabetes with microalbuminuria (4)
- Serum creatinine >2.0 mg/dL in males, >1.8 mg/dL in females (4)
- Creatinine clearance <50 mL/min (4)
- Concomitant use of potassium supplements or potassium-sparing diuretics (4)

5 WARNINGS AND PRECAUTIONS

- Hyperkalemia: Patients with decreased renal function, diabetes, proteinuria or patients who are taking ACEs and ARBs, NSAIDs or moderate CYP3A inhibitors are at increased risk. Monitor serum potassium levels and adjust dose as needed. (5.1)

6 ADVERSE REACTIONS

HFrEF Post-MI: Most common adverse reactions (>2% and more frequent than with placebo): hyperkalemia and increased creatinine. (6.1)
Hypertension: In clinical studies, adverse reactions with INSPRA were uncommon. (6.1)

To report SUSPECTED ADVERSE REACTIONS, contact Viatris at 1-877-446-3679 (1-877-4-INFO-RX) or FDA at 1-800-FDA-1088 or www.fda.gov/medwatch.

7 DRUG INTERACTIONS

- CYP3A Inhibitors: In post-MI HFrEF patients, do not exceed 25 mg once daily when used with moderate CYP3A inhibitors (e.g., verapamil, erythromycin, saquinavir, fluconazole). In patients with hypertension, initiate at 25 mg once daily. For inadequate blood pressure response, dosing may be increased to a maximum of 25 mg twice daily. (2.4, 7.1, 12.3)

FULL PRESCRIBING INFORMATION

1 INDICATIONS AND USAGE

1.1 Heart Failure Post-Myocardial Infarction

INSPRA is indicated to improve survival of stable adult patients with symptomatic heart failure with reduced ejection fraction (≤40%) (HFrEF) after an acute myocardial infarction (MI).

1.2 Hypertension

INSPRA is indicated for the treatment of hypertension in adults, to lower blood pressure. Lowering blood pressure reduces the risk of fatal and nonfatal cardiovascular (CV) events, primarily strokes and MI. These benefits have been seen in controlled trials of antihypertensive drugs from a wide variety of pharmacologic classes.

Control of high blood pressure should be part of comprehensive CV risk management, including, as appropriate, lipid control, diabetes management, antithrombotic therapy, smoking cessation, exercise, and limited sodium intake. Many patients will require more than one drug to achieve blood pressure goals. For specific advice on goals and management, see published guidelines, such as those of the National High Blood Pressure Education Program’s Joint National Committee on Prevention, Detection, Evaluation, and Treatment of High Blood Pressure (JNC).

Numerous antihypertensive drugs, from a variety of pharmacologic classes and with different mechanisms of action, have been shown in randomized controlled trials to reduce CV morbidity and mortality, and it can be concluded that it is blood pressure reduction, and not some other pharmacologic property of the drugs, that is largely responsible for those benefits. The largest and most consistent CV outcome benefit has been a reduction in the risk of stroke, but reductions in MI and CV mortality also have been seen regularly.

Elevated systolic or diastolic pressure causes increased CV risk, and the absolute risk increase per mmHg is greater at higher blood pressures, so that even modest reductions of severe hypertension can provide substantial benefit. Relative risk reduction from blood pressure reduction is similar across populations with varying absolute risk, so the absolute benefit is greater in patients who are at higher risk independent of their hypertension (for example, patients with diabetes or hyperlipidemia), and such patients would be expected to benefit from more aggressive treatment to a lower blood pressure goal.

Some antihypertensive drugs have smaller blood pressure effects (as monotherapy) in black patients, and many antihypertensive drugs have additional approved indications and effects (e.g., on angina, heart failure, or diabetic kidney disease). These considerations may guide selection of therapy.

INSPRA may be used alone or in combination with other antihypertensive agents.

2 DOSAGE AND ADMINISTRATION

2.1 Heart Failure Post-Myocardial Infarction

Initiate treatment at 25 mg once daily and titrate to the recommended dose of 50 mg once daily, preferably within 4 weeks as tolerated by the patient.

Once treatment with INSPRA has begun, adjust the dose based on the serum potassium level as shown in Table 1.

Table 1. Dose Adjustment in Heart Failure Post-MI
Serum Potassium (mEq/L) | Dose Adjustment
<5.0 | 25 mg every other day to 25 mg once daily 25 mg once daily to 50 mg once daily
5.0-5.4 | No adjustment
5.5-5.9 | 50 mg once daily to 25 mg once daily 25 mg once daily to 25 mg every other day 25 mg every other day to withhold
≥6.0 | Withhold and restart at 25 mg every other day when potassium levels fall to <5.5 mEq/L

2.2 Hypertension

The recommended starting dose of INSPRA is 50 mg administered once daily. The full therapeutic effect of INSPRA is apparent within 4 weeks. For patients with an inadequate blood pressure response to 50 mg once daily increase the dosage of INSPRA to 50 mg twice daily. Higher dosages of INSPRA are not recommended because they have no greater effect on blood pressure than 100 mg and are associated with an increased risk of hyperkalemia [see Clinical Studies (14.2)].

2.3 Recommended Monitoring

Measure serum potassium before initiating INSPRA therapy, within the first week, and at one month after the start of treatment or dose adjustment. Assess serum potassium periodically thereafter.

Check serum potassium and serum creatinine within 3-7 days of a patient initiating a moderate CYP3A inhibitor ACE inhibitors, angiotensin II blockers or nonsteroidal anti-inflammatories.

2.4 Dose Modification for Use with Moderate CYP3A Inhibitors

In post-MI HFrEF patients receiving a moderate CYP3A inhibitor (e.g., erythromycin, saquinavir, verapamil, and fluconazole), do not exceed 25 mg once daily. In patients with hypertension receiving a moderate CYP3A inhibitor, initiate at 25 mg once daily. For inadequate blood pressure response, dosing may be increased to a maximum of 25 mg twice daily [see Drug Interactions (7.1)].

3 DOSAGE FORMS AND STRENGTHS

- 25 mg tablets: yellow diamond biconvex film-coated tablets debossed with “VLE” on one side and “NSR” over “25” on the other
- 50 mg tablets: yellow diamond biconvex film-coated tablets debossed with “VLE” on one side and “NSR” over “50” on the other

4 CONTRAINDICATIONS

For All Patients

INSPRA is contraindicated in all patients with:

- serum potassium >5.5 mEq/L at initiation,
- creatinine clearance ≤30 mL/min, or
- concomitant administration of strong CYP3A inhibitors (e.g., ketoconazole, itraconazole, nefazodone, troleandomycin, clarithromycin, ritonavir, and nelfinavir) [see Drug Interactions (7.1), Clinical Pharmacology (12.3)].

For Patients Treated for Hypertension

INSPRA is contraindicated for the treatment of hypertension in patients with:

- type 2 diabetes with microalbuminuria,
- serum creatinine >2.0 mg/dL in males or >1.8 mg/dL in females,
- creatinine clearance <50 mL/min, or
- concomitant administration of potassium supplements or potassium-sparing diuretics (e.g., amiloride, spironolactone, or triamterene) [see Warnings and Precautions (5.1), Adverse Reactions (6.2), Drug Interactions (7), and Clinical Pharmacology (12.3)].

5 WARNINGS AND PRECAUTIONS

5.1 Hyperkalemia

The risk of hyperkalemia is higher in patients with impaired renal function, proteinuria, diabetes and those concomitantly treated with ACEs, ARBs, NSAIDs and moderate CYP3A inhibitors. Minimize the risk of hyperkalemia with proper patient selection and monitoring [see Dosage and Administration (2.1), Contraindications (4), Adverse Reactions (6.2), and Drug Interactions (7)]. Monitor patients for the development of hyperkalemia until the effect of INSPRA is established. Patients who develop hyperkalemia (5.5-5.9 mEq/L) may continue INSPRA therapy with proper dose adjustment. Dose reduction decreases potassium levels. Patients on moderate CYP3A inhibitors that cannot be avoided should have their dose of eplerenone reduced [see Drug Interactions (7.2)].

6 ADVERSE REACTIONS

The following adverse reactions are discussed in greater detail in other sections of the labeling:

- Hyperkalemia [see Warnings and Precautions (5.1)]

6.1 Clinical Trials Experience

Because clinical trials are conducted under widely varying conditions, adverse reaction rates observed in the clinical trials of a drug cannot be directly compared to rates in clinical trials of another drug and may not reflect the rates observed in practice.

Heart Failure Post-Myocardial Infarction

In EPHESUS, safety was evaluated in 3307 patients treated with INSPRA and 3301 placebo-treated patients. The overall incidence of adverse events reported with INSPRA (78.9%) was similar to placebo (79.5%). Adverse events occurred at a similar rate regardless of age, gender, or race. Patients discontinued treatment due to an adverse event at similar rates in either treatment group (4.4% INSPRA vs. 4.3% placebo), with the most common reasons for discontinuation being hyperkalemia, MI, and abnormal renal function.

Adverse reactions that occurred more frequently in patients treated with INSPRA than placebo were hyperkalemia (3.4% vs. 2.0%) and increased creatinine (2.4% vs. 1.5%). Discontinuations due to hyperkalemia or abnormal renal function were less than 1.0% in both groups.

Hypertension

INSPRA has been evaluated for safety in 3091 patients treated for hypertension. A total of 690 patients were treated for over 6 months and 106 patients were treated for over 1 year.

In placebo-controlled studies, the overall rates of adverse events were 47% with INSPRA and 45% with placebo. Adverse events occurred at a similar rate regardless of age, gender, or race. Therapy was discontinued due to an adverse event in 3% of patients treated with INSPRA and 3% of patients given placebo. The most common reasons for discontinuation of INSPRA were headache, dizziness, angina pectoris/MI, and increased GGT.

Gynecomastia and abnormal vaginal bleeding were reported with INSPRA but not with placebo. The rates increased with increasing duration of therapy.

6.2 Postmarketing Experience

The following adverse reactions have been identified during postapproval use of INSPRA. Because these reactions are reported voluntarily from a population of uncertain size, it is not always possible to reliably estimate their frequency or establish a causal relationship to drug exposure.

Skin: angioedema, rash

6.3 Clinical Laboratory Test Findings

Heart Failure Post-Myocardial Infarction

Creatinine: Increases of more than 0.5 mg/dL were reported for 6.5% of patients administered INSPRA and for 4.9% of placebo-treated patients.

Potassium: In EPHESUS [see Clinical Studies (14.1)], the frequencies of patients with changes in potassium (<3.5 mEq/L or >5.5 mEq/L or ≥6.0 mEq/L) receiving INSPRA compared with placebo are displayed in Table 2.

Table 2. Hypokalemia (<3.5 mEq/L) or Hyperkalemia (>5.5 or ≥6.0 mEq/L) in EPHESUS
Potassium (mEq/L) | INSPRA (N=3251) n (%) | Placebo (N=3237) n (%)
<3.5 | 273 (8.4) | 424 (13.1)
>5.5 | 508 (15.6) | 363 (11.2)
≥6.0 | 180 (5.5) | 126 (3.9)

Rates of hyperkalemia increased with decreasing renal function.

Table 3. Rates of Hyperkalemia (>5.5 mEq/L) in EPHESUS by Baseline Creatinine Clearance*
Baseline Creatinine Clearance | INSPRA (N=508) n (%) | Placebo (N=363) n (%)
≤30 mL/min | 160 (32) | 82 (23)
31-50 mL/min | 122 (24) | 46 (13)
51-70 mL/min | 86 (17) | 48 (13)
>70 mL/min | 56 (11) | 32 (9)
* Estimated using the Cockroft-Gault formula.

The rates of hyperkalemia in EPHESUS in the INSPRA-treated group vs. placebo were increased in patients with proteinuria (16% vs 11%), diabetes (18% vs. 13%) or both (26% vs. 16%).

Hypertension

Potassium: In placebo-controlled fixed-dose studies, the mean increases in serum potassium were dose-related and are shown in Table 4 along with the frequencies of values >5.5 mEq/L.

Table 4. Increases in Serum Potassium in the Placebo-Controlled, Fixed-Dose Hypertension Studies of INSPRA
 |  | Mean Increase mEq/L | % >5.5 mEq/L
Daily Dosage | n
Placebo | 194 | 0 | 1
25 | 97 | 0.08 | 0
50 | 245 | 0.14 | 0
100 | 193 | 0.09 | 1

7 DRUG INTERACTIONS

7.1 CYP3A Inhibitors

Eplerenone metabolism is predominantly mediated via CYP3A. Do not use INSPRA with drugs that are strong inhibitors of CYP3A [see Contraindications (4) and Clinical Pharmacology (12.3)].

In post-MI HFrEF patients taking a moderate CYP3A inhibitor, do not exceed 25 mg once daily. In patients with hypertension taking a moderate CYP3A inhibitor, initiate at 25 mg once daily. For inadequate blood pressure response, dosing may be increased to a maximum of 25 mg twice daily [see Dosage and Administration (2.3, 2.4) and Clinical Pharmacology (12.3)].

7.2 ACE Inhibitors and Angiotensin II Receptor Antagonists

The risk of hyperkalemia increases when eplerenone is used in combination with an ACE inhibitor and/or an ARB. A close monitoring of serum potassium and renal function is recommended, especially in patients at risk for impaired renal function, e.g., the elderly [see Warnings and Precautions (5.1)].

7.3 Lithium

A drug interaction study of eplerenone with lithium has not been conducted. Lithium toxicity has been reported in patients receiving lithium concomitantly with diuretics and ACE inhibitors. Serum lithium levels should be monitored frequently if INSPRA is administered concomitantly with lithium.

7.4 Nonsteroidal Anti-Inflammatory Drugs (NSAIDs)

A drug interaction study of eplerenone with an NSAID has not been conducted. The administration of other potassium-sparing antihypertensives with NSAIDs has been shown to reduce the antihypertensive effect in some patients and result in severe hyperkalemia in patients with impaired renal function. Therefore, when INSPRA and NSAIDs are used concomitantly, monitor blood pressure and serum potassium levels.

8 USE IN SPECIFIC POPULATIONS

8.1 Pregnancy

Risk Summary

The available data from published case reports on eplerenone use during pregnancy are insufficient to establish a drug-associated risk of major birth defects, miscarriage, adverse maternal or fetal outcomes (see Clinical Considerations). In animal studies, no adverse developmental effects were observed when eplerenone was administered to pregnant rats and rabbits during organogenesis at exposures 32 and 31 times, respectively the human exposure at the 100 mg/day therapeutic dose.

The estimated background risk of major birth defects and miscarriage for the indicated population are unknown. In the U.S. general population, the estimated background risk of major birth defects and miscarriage in clinically recognized pregnancies is 2-4% and 15-20%, respectively.

Clinical Considerations

Disease-Associated Maternal and/or Embryo/Fetal Risk

Hypertension in pregnancy increases the maternal risk for pre-eclampsia, gestational diabetes, premature delivery, and delivery complications (e.g., need for cesarean section, and post-partum hemorrhage). Hypertension increases the fetal risk for intrauterine growth restriction and intrauterine death. Pregnant women with hypertension should be carefully monitored and managed accordingly.

Pregnant women with heart failure are at increased risk for preterm birth. Stroke volume and heart rate increase during pregnancy, increasing cardiac output, especially during the first trimester. Clinical classification of heart disease may worsen with pregnancy and lead to maternal death. Closely monitor pregnant patients for destabilization of their heart failure.

Data

Animal Data

Embryo-fetal development studies were conducted with doses up to 1000 mg/kg/day in rats and 300 mg/kg/day in rabbits (exposures up to 32 and 31 times the human AUC for the 100 mg/day therapeutic dose, respectively) administered during organogenesis. No teratogenic effects were seen in rats or rabbits, although decreased rat fetal weights were observed, and decreased body weight in maternal rabbits and increased rabbit fetal resorptions and post-implantation loss were observed at the highest administered dosages.

In a pre- and postnatal development study, pregnant rats were administered eplerenone at doses up to 1000 mg/kg/day from Gestation Day 6 through Lactation Day 20. Decreased pup weights were observed beginning at birth at 1000 mg/kg/day.

8.2 Lactation

Risk Summary

There are no human data available on whether eplerenone is present in human milk, or has effects on breastfed infants or on milk production. Eplerenone was present in the milk of lactating rats. When a drug is present in animal milk, it is likely that the drug will be present in human milk.

8.3 Females and Males of Reproductive Potential

Infertility

Based on animal data, use of INSPRA may compromise male fertility. In mature rats, male fertility was decreased with eplerenone exposure at 17 times the 100 mg/day human therapeutic dose. Reversibility of effects was not evaluated [see Nonclinical Toxicology (13.1)].

8.4 Pediatric Use

The safety and effectiveness of INSPRA for treatment of hypertension have not been established in pediatric patients. In a 10-week study of 304 hypertensive pediatric patients ages 4 to 16 years treated with INSPRA up to 100 mg per day, doses that produced exposure similar to that in adults, INSPRA did not lower blood pressure effectively. In this study and in a 1-year pediatric safety study in 149 patients (age range 5 to 17 years), the incidence of reported adverse events was similar to that of adults. INSPRA was not studied for treatment of hypertension in pediatric patients younger than 4 years of age because the study in older pediatric patients did not demonstrate effectiveness.

The safety and effectiveness of INSPRA have not been established in pediatric patients with heart failure.

8.5 Geriatric Use

Heart Failure Post-Myocardial Infarction

Of the total number of patients in EPHESUS, 3340 (50%) were 65 and over, while 1326 (20%) were 75 and over. Patients greater than 75 years did not appear to benefit from the use of INSPRA [see Clinical Studies (14.1)].

No differences in overall incidence of adverse events were observed between elderly and younger patients. However, due to age-related decreases in creatinine clearance, the incidence of laboratory-documented hyperkalemia was increased in patients 65 and older [see Warnings and Precautions (5.1)].

Hypertension

Of the total number of subjects in clinical hypertension studies of INSPRA, 1123 (23%) were 65 and over, while 212 (4%) were 75 and over. No overall differences in safety or effectiveness were observed between elderly subjects and younger subjects, however due to age-related decreases in creatine clearance, the risk of hyperkalemia may be increased [see Warnings and Precautions (5.1)].

10 OVERDOSAGE

No cases of human overdosage with eplerenone have been reported. Lethality was not observed in mice, rats, or dogs after single oral doses that provided Cmax exposures at least 25 times higher than in humans receiving eplerenone 100 mg/day. Dogs showed emesis, salivation, and tremors at a Cmax 41 times the human therapeutic Cmax, progressing to sedation and convulsions at higher exposures.

The most likely manifestation of human overdosage would be anticipated to be hypotension or hyperkalemia. Eplerenone cannot be removed by hemodialysis. Eplerenone has been shown to bind extensively to charcoal. If symptomatic hypotension should occur, supportive treatment should be instituted. If hyperkalemia develops, standard treatment should be initiated.

11 DESCRIPTION

INSPRA contains eplerenone, a blocker of aldosterone binding at the mineralocorticoid receptor.

Eplerenone is chemically described as Pregn-4-ene-7,21-dicarboxylic acid, 9,11-epoxy-17-hydroxy-3-oxo-, γ-lactone, methyl ester, (7α,11α,17α)-. Its empirical formula is C24H30O6 and it has a molecular weight of 414.50. The structural formula of eplerenone is represented below:

Eplerenone is an odorless, white to off-white crystalline powder. It is very slightly soluble in water, with its solubility essentially pH-independent. The octanol/water partition coefficient of eplerenone is approximately 7.1 at pH 7.0.

INSPRA tablets for oral administration contain 25 mg or 50 mg of eplerenone and the following inactive ingredients: croscarmellose sodium, hypromellose, lactose monohydrate, magnesium stearate, microcrystalline cellulose, polyethylene glycol, polysorbate 80, red iron oxide, sodium lauryl sulfate, talc, titanium dioxide, and yellow iron oxide.

12 CLINICAL PHARMACOLOGY

12.1 Mechanism of Action

Eplerenone binds to the mineralocorticoid receptor and blocks the binding of aldosterone, a component of the renin-angiotensin-aldosterone-system (RAAS). Aldosterone synthesis, which occurs primarily in the adrenal gland, is modulated by multiple factors, including angiotensin II and non-RAAS mediators such as adrenocorticotropic hormone (ACTH) and potassium. Aldosterone binds to mineralocorticoid receptors in both epithelial (e.g., kidney) and nonepithelial (e.g., heart, blood vessels, and brain) tissues and increases blood pressure through induction of sodium reabsorption and possibly other mechanisms.

Eplerenone has been shown to produce sustained increases in plasma renin and serum aldosterone, consistent with inhibition of the negative regulatory feedback of aldosterone on renin secretion. The resulting increased plasma renin activity and aldosterone circulating levels do not overcome the effects of eplerenone.

Eplerenone selectively binds to human mineralocorticoid receptors relative to its binding to recombinant human glucocorticoid, progesterone, and androgen receptors.

12.2 Pharmacodynamics

There was no significant change in average heart rate among patients treated with INSPRA in the combined clinical studies. No consistent effects of INSPRA on heart rate, QRS duration, or PR or QT interval were observed in 147 normal subjects evaluated for electrocardiographic changes during pharmacokinetic studies.

12.3 Pharmacokinetics

Eplerenone is cleared predominantly by cytochrome P450 (CYP) 3A4 metabolism, with an elimination half-life of 3 to 6 hours. Steady state is reached within 2 days. Absorption is not affected by food. Inhibitors of CYP3A (e.g., ketoconazole, saquinavir) increase blood levels of eplerenone.

Absorption and Distribution

Mean peak plasma concentrations of eplerenone are reached approximately 1.5 to 2 hours following oral administration. Absorption is not affected by food. The absolute bioavailability of eplerenone is 69% following administration of a 100 mg oral tablet. Both peak plasma levels (Cmax) and area under the curve (AUC) are dose proportional for doses of 25 mg to 100 mg and less than proportional at doses above 100 mg. Upon repeat dosing, steady state levels are reached within 2 days.

The plasma protein binding of eplerenone is about 50% and it is primarily bound to alpha 1-acid glycoproteins. The apparent volume of distribution at steady state ranged from 42 to 90 L. Eplerenone does not preferentially bind to red blood cells.

Metabolism and Excretion

Eplerenone metabolism is primarily mediated via CYP3A4. No active metabolites of eplerenone have been identified in human plasma.

Less than 5% of an eplerenone dose is recovered as unchanged drug in the urine and feces. Following a single oral dose of radiolabeled drug, approximately 32% of the dose was excreted in the feces and approximately 67% was excreted in the urine. The elimination half-life of eplerenone is approximately 3 to 6 hours. The apparent plasma clearance is approximately 10 L/hr.

Age, Gender, and Race

The pharmacokinetics of eplerenone at a dose of 100 mg once daily has been investigated in the elderly (≥65 years), in males and females, and in Blacks. At steady state, elderly subjects had increases in Cmax (22%) and AUC (45%) compared with younger subjects (18 to 45 years). The pharmacokinetics of eplerenone did not differ significantly between males and females. At steady state, Cmax was 19% lower and AUC was 26% lower in Blacks [see Dosage and Administration (2.4) and Use in Specific Populations (8.5)].

Renal Impairment

The pharmacokinetics of eplerenone was evaluated in patients with varying degrees of renal impairment and in patients undergoing hemodialysis. Compared with control subjects, steady state AUC and Cmax were increased by 38% and 24%, respectively, in patients with severe renal impairment and were decreased by 26% and 3%, respectively, in patients undergoing hemodialysis. No correlation was observed between plasma clearance of eplerenone and creatinine clearance. Eplerenone is not removed by hemodialysis [see Warnings and Precautions (5.1)].

Hepatic Impairment

The pharmacokinetics of eplerenone 400 mg has been investigated in patients with moderate (Child-Pugh Class B) hepatic impairment and compared with normal subjects. Steady state Cmax and AUC of eplerenone were increased by 3.6% and 42%, respectively.

Heart Failure

The pharmacokinetics of eplerenone 50 mg was evaluated in 8 patients with heart failure (NYHA classification II–IV) and 8 matched (gender, age, weight) healthy controls. Compared with the controls, steady state AUC and Cmax in patients with stable heart failure were 38% and 30% higher, respectively.

Drug-Drug Interactions

Eplerenone is metabolized primarily by CYP3A4. Inhibitors of CYP3A cause increased exposure [see Drug Interactions (7.1)].

Drug-drug interaction studies were conducted with a 100 mg dose of eplerenone.

Following a single dose of INSPRA 100 mg and CYP3A inhibitor ketoconazole 200 mg twice a day, eplerenone’s Cmax was 1.7-fold and AUC was 5.4-fold compared with eplerenone alone.

Administration of eplerenone with moderate CYP3A inhibitors (e.g., erythromycin 500 mg BID, verapamil 240 mg once daily, saquinavir 1200 mg three times a day, fluconazole 200 mg once daily) resulted in increases in Cmax of eplerenone ranging from 40% to 60% and AUC from 100% to 190%.

Grapefruit juice caused a 25% increase in exposure.

Eplerenone is not an inhibitor of CYP1A2, CYP3A4, CYP2C19, CYP2C9, or CYP2D6. Eplerenone did not inhibit the metabolism of amiodarone, amlodipine, astemizole, chlorzoxazone, cisapride, dexamethasone, dextromethorphan, diclofenac, 17α-ethinyl estradiol, fluoxetine, losartan, lovastatin, mephobarbital, methylphenidate, methylprednisolone, metoprolol, midazolam, nifedipine, phenacetin, phenytoin, simvastatin, tolbutamide, triazolam, verapamil, or warfarin in vitro. Eplerenone is not a substrate or an inhibitor of P-Glycoprotein at clinically relevant doses.

No clinically significant drug-drug pharmacokinetic interactions were observed when eplerenone was administered with cisapride, cyclosporine, digoxin, glyburide, midazolam, oral contraceptives (norethindrone/ethinyl estradiol), simvastatin, or warfarin. St. John’s wort (a CYP3A inducer) caused a small (about 30%) decrease in eplerenone AUC.

No significant changes in eplerenone pharmacokinetics were observed when eplerenone was administered with aluminum- and magnesium-containing antacids.

13 NONCLINICAL TOXICOLOGY

13.1 Carcinogenesis, Mutagenesis, Impairment of Fertility

Eplerenone was non-genotoxic in a battery of assays including in vitro bacterial mutagenesis (Ames test in Salmonella spp. and E. coli), in vitro mammalian cell mutagenesis (mouse lymphoma cells), in vitro chromosomal aberration (Chinese hamster ovary cells), in vivo rat bone marrow micronucleus formation, and in vivo/ex vivo unscheduled DNA synthesis in rat liver.

There was no drug-related tumor response in heterozygous P53 deficient mice when tested for 6 months at dosages up to 1000 mg/kg/day (systemic AUC exposures up to 9 times the exposure in humans receiving the 100 mg/day therapeutic dose). Statistically significant increases in benign thyroid tumors were observed after 2 years in both male and female rats when administered eplerenone 250 mg/kg/day (highest dose tested) and in male rats only at 75 mg/kg/day. These dosages provided systemic AUC exposures approximately 2 to 12 times higher than the average human therapeutic exposure at 100 mg/day. Repeat dose administration of eplerenone to rats increases the hepatic conjugation and clearance of thyroxin, which results in increased levels of TSH by a compensatory mechanism. Drugs that have produced thyroid tumors by this rodent-specific mechanism have not shown a similar effect in humans.

Male rats treated with eplerenone at 1000 mg/kg/day for 10 weeks (AUC 17 times that at the 100 mg/day human therapeutic dose) had decreased weights of seminal vesicles and epididymides and slightly decreased fertility. Dogs administered eplerenone at dosages of 15 mg/kg/day and higher (AUC 5 times that at the 100 mg/day human therapeutic dose) had dose-related prostate atrophy. The prostate atrophy was reversible after daily treatment for 1 year at 100 mg/kg/day. Dogs with prostate atrophy showed no decline in libido, sexual performance, or semen quality. Testicular weight and histology were not affected by eplerenone in any test animal species at any dosage.

14 CLINICAL STUDIES

14.1 Heart Failure Post-Myocardial Infarction

The eplerenone post-acute myocardial infarction heart failure efficacy and survival study (EPHESUS) was a multinational, multicenter, double-blind, randomized, placebo-controlled study in patients clinically stable 3 to 14 days after an acute MI with LV dysfunction (as measured by left ventricular ejection fraction [LVEF] ≤40%) and either diabetes or clinical evidence of HF (pulmonary congestion by exam or chest x-ray or S3). Patients with HF of valvular or congenital etiology, patients with unstable post-infarct angina, and patients with serum potassium >5.0 mEq/L or serum creatinine >2.5 mg/dL were to be excluded. Patients were allowed to receive standard post-MI drug therapy and to undergo revascularization by angioplasty or coronary artery bypass graft surgery.

Patients randomized to INSPRA were given an initial dose of 25 mg once daily and titrated to the target dose of 50 mg once daily after 4 weeks if serum potassium was <5.0 mEq/L. Dosage was reduced or suspended anytime during the study if serum potassium levels were ≥5.5 mEq/L [see Dosage and Administration (2.1)].

EPHESUS randomized 6,632 patients (9.3% U.S.) at 671 centers in 27 countries. The study population was primarily white (90%, with 1% Black, 1% Asian, 6% Hispanic, 2% other) and male (71%). The mean age was 64 years (range, 22 to 94 years). The majority of patients had pulmonary congestion (75%) by exam or x-ray and were Killip Class II (64%). The mean ejection fraction was 33%. The average time to enrollment was 7 days post-MI. Medical histories prior to the index MI included hypertension (60%), coronary artery disease (62%), dyslipidemia (48%), angina (41%), type 2 diabetes (30%), previous MI (27%), and HF (15%).

The mean dose of INSPRA was 43 mg/day. Patients also received standard care including aspirin (92%), ACE inhibitors (90%), beta-blockers (83%), nitrates (72%), loop diuretics (66%), or HMG-CoA reductase inhibitors (60%).

Patients were followed for an average of 16 months (range, 0 to 33 months). The ascertainment rate for vital status was 99.7%.

The co-primary endpoints for EPHESUS were (1) the time to death from any cause, and (2) the time to first occurrence of either cardiovascular mortality [defined as sudden cardiac death or death due to progression of HF, stroke, or other CV causes] or CV hospitalization (defined as hospitalization for progression of HF, ventricular arrhythmias, acute MI, or stroke).

For the co-primary endpoint for death from any cause, there were 478 deaths in the INSPRA group (14.4%) and 554 deaths in the placebo group (16.7%). The risk of death with INSPRA was reduced by 15% [hazard ratio equal to 0.85 (95% confidence interval 0.75 to 0.96; p = 0.008 by log rank test)]. Kaplan-Meier estimates of all-cause mortality are shown in Figure 1 and the components of mortality are provided in Table 5.

Figure 1. Kaplan-Meier Estimates of All-Cause Mortality

Table 5. Components of All-Cause Mortality in EPHESUS
 | INSPRA (N=3319) n (%) | Placebo (N=3313) n (%) | Hazard Ratio | p-value
Death from any cause | 478 (14.4) | 554 (16.7) | 0.85 | 0.008
CV Death | 407 (12.3) | 483 (14.6) | 0.83 | 0.005
Non-CV Death | 60 (1.8) | 54 (1.6)
Unknown or unwitnessed death | 11 (0.3) | 17 (0.5)

Most CV deaths were attributed to sudden death, acute MI, and HF.

The time to first event for the co-primary endpoint of CV death or hospitalization, as defined above, was longer in the INSPRA group (hazard ratio 0.87, 95% confidence interval 0.79 to 0.95, p = 0.002). An analysis that included the time to first occurrence of CV mortality and all CV hospitalizations (atrial arrhythmia, angina, CV procedures, progression of HF, MI, stroke, ventricular arrhythmia, or other CV causes) showed a smaller effect with a hazard ratio of 0.92 (95% confidence interval 0.86 to 0.99; p = 0.028). The combined endpoints, including combined all-cause hospitalization and mortality were driven primarily by CV mortality. The combined endpoints in EPHESUS, including all-cause hospitalization and all-cause mortality, are presented in Table 6.

Table 6. Rates of Death or Hospitalization in EPHESUS
Event | INSPRA n (%) | Placebo n (%)
CV death or hospitalization for progression of HF, stroke, MI or ventricular arrhythmia [Co-Primary Endpoint.] | 885 (26.7) | 993 (30.0)
Death; Hospitalization | 407 (12.3); 606 (18.3) | 483 (14.6); 649 (19.6)
CV death or hospitalization for progression of HF, stroke, MI, ventricular arrhythmia, atrial arrhythmia, angina, CV procedures, or other CV causes (PVD; Hypotension) | 1516 (45.7) | 1610 (48.6)
Death; Hospitalization | 407 (12.3); 1281 (38.6) | 483 (14.6); 1307 (39.5)
All-cause death or hospitalization; Death; Hospitalization | 1734 (52.2); 478 (14.4); 1497 (45.1) | 1833 (55.3); 554 (16.7); 1530 (46.2)

Mortality hazard ratios varied for some subgroups as shown in Figure 2. Mortality hazard ratios appeared favorable for INSPRA for both genders and for all races or ethnic groups, although the numbers of non-Caucasians were low (648, 10%). Patients with diabetes without clinical evidence of HF and patients greater than 75 years did not appear to benefit from the use of INSPRA. Such subgroup analyses must be interpreted cautiously.

Figure 2. Hazard Ratios of All-Cause Mortality by Subgroups

Analyses conducted for a variety of CV biomarkers did not confirm a mechanism of action by which mortality was reduced.

14.2 Hypertension

The safety and efficacy of INSPRA have been evaluated alone and in combination with other antihypertensive agents in clinical studies of 3091 hypertensive patients. The studies included 46% women, 14% Blacks, and 22% elderly (age ≥65). The studies excluded patients with elevated baseline serum potassium (>5.0 mEq/L) and elevated baseline serum creatinine (generally >1.5 mg/dL in males and >1.3 mg/dL in females).

Two fixed-dose, placebo-controlled, 8- to 12-week monotherapy studies in patients with baseline diastolic blood pressures of 95 to 114 mmHg were conducted to assess the antihypertensive effect of INSPRA. In these two studies, 611 patients were randomized to INSPRA and 140 patients to placebo. Patients received INSPRA in doses of 25 mg to 400 mg daily as either a single daily dose or divided into two daily doses. The mean placebo-subtracted reductions in trough cuff blood pressure achieved by INSPRA in these studies at doses up to 200 mg are shown in Figures 3 and 4.

Figure 3. INSPRA Dose Response – Trough Cuff SBP Placebo-Subtracted Adjusted Mean Change from Baseline In Hypertension Studies

Figure 4. INSPRA Dose Response – Trough Cuff DBP Placebo-Subtracted Adjusted Mean Change from Baseline in Hypertension Studies

Patients treated with INSPRA 50 mg to 200 mg daily experienced significant decreases in sitting systolic and diastolic blood pressure at trough with differences from placebo of 6-13 mmHg (systolic) and 3-7 mmHg (diastolic). These effects were confirmed by assessments with 24-hour ambulatory blood pressure monitoring (ABPM). In these studies, assessments of 24-hour ABPM data demonstrated that INSPRA, administered once or twice daily, maintained antihypertensive efficacy over the entire dosing interval. However, at a total daily dose of 100 mg, INSPRA administered as 50 mg twice per day produced greater trough cuff (4/3 mmHg) and ABPM (2/1 mmHg) blood pressure reductions than 100 mg given once daily.

Blood pressure lowering was apparent within 2 weeks from the start of therapy with INSPRA, with maximal antihypertensive effects achieved within 4 weeks. Stopping INSPRA following treatment for 8 to 24 weeks in six studies did not lead to adverse event rates in the week following withdrawal of INSPRA greater than following placebo or active control withdrawal. Blood pressures in patients not taking other antihypertensives rose 1 week after withdrawal of INSPRA by about 6/3 mmHg, suggesting that the antihypertensive effect of INSPRA was maintained through 8 to 24 weeks.

Blood pressure reductions with INSPRA in the two fixed-dose monotherapy studies and other studies using titrated doses, as well as concomitant treatments, were not significantly different when analyzed by age, gender, or race with one exception. In a study in patients with low renin hypertension, blood pressure reductions in Blacks were smaller than those in whites during the initial titration period with INSPRA.

INSPRA has been studied concomitantly with treatment with ACE inhibitors, ARB, calcium channel blockers, beta-blockers, and hydrochlorothiazide. When administered concomitantly with one of these drugs, INSPRA usually produced its expected antihypertensive effects.

16 HOW SUPPLIED/STORAGE AND HANDLING

INSPRA Tablets are yellow, diamond biconvex, and film-coated. They are debossed with “VLE” on one side. They are supplied as follows:

Dose | Deboss Side 2 | NDC 58151-xxx-xx
Dose | Deboss Side 2 | Bottle/30
25 mg | NSR 25 | 142-93
50 mg | NSR 50 | 143-93

Store at 25°C (77°F); excursions permitted to 15-30°C (59-86°F) [See USP Controlled Room Temperature].

17 PATIENT COUNSELING INFORMATION

Advise patients receiving INSPRA:

- Not to use potassium supplements or salt substitutes containing potassium without consulting the prescribing physician [see Warnings and Precautions (5.1)].
- To call their physician if they experience dizziness, diarrhea, vomiting, rapid or irregular heartbeat, lower extremity edema, or difficulty breathing [see Warnings and Precautions (5.1)].

Distributed by:
Viatris Specialty LLC
Morgantown, WV 26505 U.S.A.

© 2025 Viatris Inc.

INSPRA is a registered trademark of UPJOHN US 2 LLC, a Viatris Company.

UPJ:INSPRA:R2

PRINCIPAL DISPLAY PANEL – 25 mg

NDC 58151-142-93

INSPRA®
(eplerenone) tablets

25 mg

30 Tablets

Rx only

Store at 25°C (77°F);
excursions permitted to
15-30°C (59-86°F)
[see USP Controlled
Room Temperature].

Dispense in tight (USP),
child-resistant containers.

DOSAGE AND USE
See accompanying
prescribing information.
Each tablet contains
25 mg eplerenone.

Distributed by:
Viatris Specialty LLC
Morgantown, WV 26505 U.S.A.

© 2023 Viatris Inc.

RUPJ142H

PRINCIPAL DISPLAY PANEL – 50 mg

NDC 58151-143-93

INSPRA®
(eplerenone) tablets

50 mg

30 Tablets

Rx only

Store at 25°C (77°F);
excursions permitted to
15-30°C (59-86°F)
[see USP Controlled
Room Temperature].

Dispense in tight (USP),
child-resistant containers.

DOSAGE AND USE
See accompanying
prescribing information.
Each tablet contains
50 mg eplerenone.

Distributed by:
Viatris Specialty LLC
Morgantown, WV 26505 U.S.A.

© 2023 Viatris Inc.

RUPJ143H